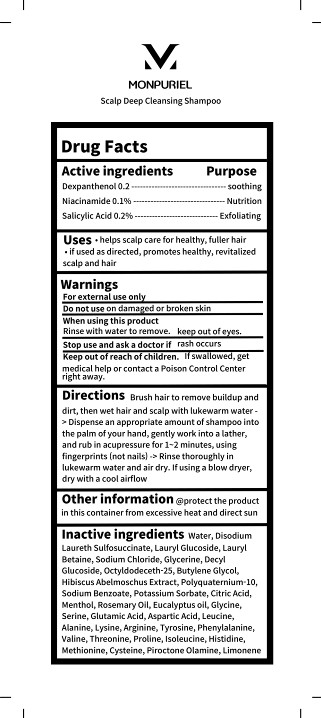 DRUG LABEL: MONPURIEL Scalp deep cleansing-shampoo
NDC: 83472-522 | Form: SHAMPOO
Manufacturer: Y2K Co., Ltd.
Category: otc | Type: HUMAN OTC DRUG LABEL
Date: 20240104

ACTIVE INGREDIENTS: DEXPANTHENOL 0.2 g/100 mL; NIACINAMIDE 0.1 g/100 mL; SALICYLIC ACID 0.2 g/100 mL
INACTIVE INGREDIENTS: WATER; DISODIUM LAURETH SULFOSUCCINATE; LAURYL GLUCOSIDE; CITRIC ACID MONOHYDRATE; SODIUM CHLORIDE; SODIUM BENZOATE; POTASSIUM SORBATE; ROSEMARY OIL; GLYCINE; SERINE; GLUTAMIC ACID; ASPARTIC ACID; LEUCINE; BUTYLENE GLYCOL; MENTHOL; EUCALYPTUS OIL; VALINE; HISTIDINE; METHIONINE; ALANINE; PHENYLALANINE; ISOLEUCINE; PIROCTONE OLAMINE; PROLINE; TYROSINE; CYSTEINE; LIMONENE, (+)-; ARGININE; THREONINE; LYSINE; POLYQUATERNIUM-10 (20000 MPA.S AT 2%); ABELMOSCHUS MANIHOT WHOLE; LAURYL BETAINE; DECYL GLUCOSIDE; GLYCERIN; OCTYLDODECETH-25

83472-522 MONPURIEL Scalp deep cleansing shampoo

Active Ingredients

Dexpanthenol 0.2

Niacinamide 0.1%

Salicylic Acid 0.2%

Purposes

Dexpanthenol 0.2-------------------------------------- soothing

Niacinamide 0.1%.............................................Nutrition

Salicylic Acid 0.2%---------------------------------- Exfoliating

Uses

• helps scalp care for healthy, fuller hair

• if used as directed, promotes healthy, revitalized

scalp and hair

Warnings

For external use only

Warnings

Do not use on damaged or broken skin

Warnings

Keep out of reach of children.

If swallowed, get medical help or contact a Poison Control Center right away.

Warnings

Stop use and ask a doctor if rash occurs

Warnings

When using this product

Rinse with water to remove, keep out of eyes.

Directions

Brush hair to remove buildup and dirt, then wet hair and scalp with lukewarm water

-> Dispense an appropriate amount of shampoo into the palm of your hand, gently work into a lather,

and rub in acupressure for 1~2 minutes, using fingerprints (not nails)

-> Rinse thoroughly in lukewarm water and air dry. If using a blow dryer, dry with a cool airflow

Inactive Ingredients

Water, Disodium Laureth Sulfosuccinate, Lauryl Glucoside, Lauryl Betaine, Sodium Chloride, Glycerine, Decyl Glucoside, Octyldodeceth-25, Butylene Glycol, Hibiscus Abelmoschus Extract, Polyquaternium-10, Sodium Benzoate, Potassium Sorbate,

Citric Acid, Menthol, Rosemary Oil, Eucalyptus oil, Glycine, Serine, Glutamic Acid, Aspartic Acid, Leucine, Alanine, Lysine, Arginine, Tyrosine, Phenylalanine, Valine, Threonine, Proline, Isoleucine, Histidine, Methionine, Cysteine, Piroctone Olamine, Limonene